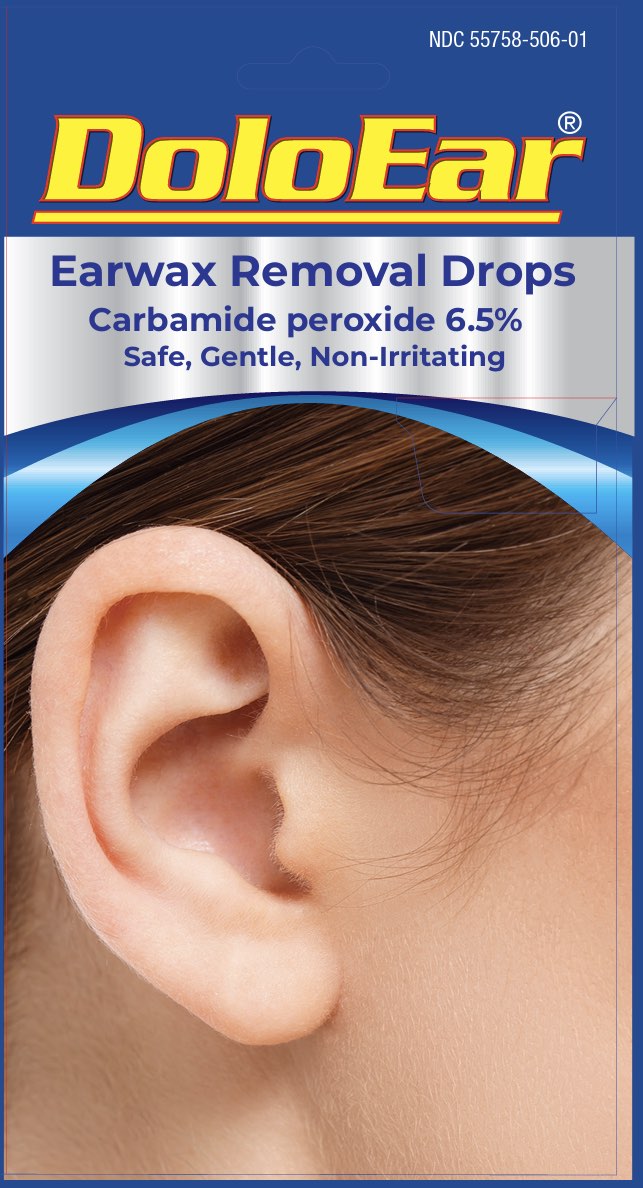 DRUG LABEL: DoloEar
NDC: 55758-506 | Form: LIQUID
Manufacturer: Pharmadel LLC
Category: otc | Type: HUMAN OTC DRUG LABEL
Date: 20250529

ACTIVE INGREDIENTS: CARBAMIDE PEROXIDE 6.5 g/100 mL
INACTIVE INGREDIENTS: GLYCERIN; WATER

DoloEar (WP)(DA)

Active Ingredient and Purpose

.

Active ingredient | Purpose
Carbamide peroxide 6.5%............... | Earwax removal aid

Uses

For occasional use as an aid to loosen and remove excessive earwax.

Warnings

Ask a doctor before use if you have

- ear drainage or discharge
- ear pain
- irritation or rash in the ear
- dizziness
- an injury or perforation (hole) of the ear drum
- recently had ear surgery

When using this product

avoid contact with the eyes.

Stop use and ask your doctor if

- you need to use for more than 4 days
- excessive earwax remains after use of this product

Directions

- FOR USE IN THE EAR ONLY
- adults and children over 12 years of age: tilt head sideways and place 5 to 10 drops into ear. Tip of applicator should not enter ear canal. Keep drops in ear for several minutes by keeping head tilted or placing cotton in the ear. Use twice daily for up to 4 days if needed, or as directed by a doctor. Any wax remaining after treatment may be removed by gently flushing the ear with warm water, using a soft rubber bulb ear syringe.
- children under 12 years of age: consult a doctor

Other information

- Store in a cool dry place
- do not use if clear seal over dropper is torn, broken, or missing

Inactive ingredients

glycerin, water

Questions or comments?

+1-866-359-3478 (M-F) 9 AM to 5 PM EST or www.pharmadel.com

Dist. by/ por:

PHARMADEL LLC

New Castle, DE 19720

+1-866-359-3478

www.pharmadel.com